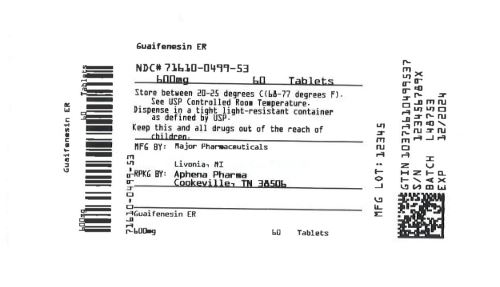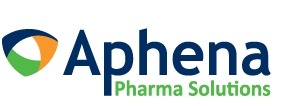 DRUG LABEL: Mucus Relief
NDC: 71610-499 | Form: TABLET, EXTENDED RELEASE
Manufacturer: Aphena Pharma Solutions - Tennessee, LLC
Category: otc | Type: Human OTC Drug Label
Date: 20210503

ACTIVE INGREDIENTS: GUAIFENESIN 600 mg/1 1
INACTIVE INGREDIENTS: CARBOMER HOMOPOLYMER, UNSPECIFIED TYPE; HYPROMELLOSE, UNSPECIFIED; CELLULOSE, MICROCRYSTALLINE; POVIDONE, UNSPECIFIED

MUCUS RELIEF
Guaifenesin Extended-Release Tablets 600 mg

ACTIVE INGREDIENT(in each extended-release tablet)

Guaifenesin 600 mg

PURPOSE

Expectorant

USE(S)

helps loosen phlegm (mucus) and thin bronchial secretions to rid the bronchial passageways of bothersome mucus and make coughs more productive

WARNING

.

DO NOT USE

for children under 12 years of age

ASK A DOCTOR BEFORE USE IF YOU HAVE

- persistent or chronic cough such as occurs with smoking, asthma, chronic bronchitis, or emphysema
- cough accompanied by too much phlegm (mucus)

STOP USE AND ASK A DOCTOR IF

- cough lasts more than 7 days, comes back, or occurs with fever, rash, or persistent headache. These could be signs of a serious illness.

IF PREGNANT OR BREAST-FEEDING,

ask a health professional before use.

KEEP OUT OF REACH OF CHILDREN

In case of overdose, get medical help or contact a Poison Control Center right away (1-800-222-1222).

DIRECTIONS

- do not crush, chew, or break tablet
- take with a full glass of water
- this product can be administered without regard for the timing of meals
- adults and children 12 years of age and over: 1 or 2 tablets every 12 hours.
- Do not exceed 4 tablets in 24 hours.
- children under 12 years of age: do not use

OTHER INFORMATION

- tamper evident: do not use if seal on the bottle printed "SEALED for YOU PROTECTION" is broken or missing.
- store between 20 to 25°C (68 to 77°F)

INACTIVE INGREDIENTS

carbomer homopolymer, hypromellose, microcrystalline cellulose, povidone

QUESTIONS?

1-800-616-2471

You may also report side effects to this phone number.

Repackaging Information

Please reference the How Supplied section listed above for a description of individual tablets. This drug product has been received by Aphena Pharma - TN in a manufacturer or distributor packaged configuration and repackaged in full compliance with all applicable cGMP regulations. The package configurations available from Aphena are listed below:

Count | 600 mg
12 | 71610-499-12
60 | 71610-499-53

Store between 20°-25°C (68°-77°F). See USP Controlled Room Temperature. Dispense in a tight light-resistant container as defined by USP. Keep this and all drugs out of the reach of children.

Repackaged by:
Cookeville, TN 38506
20201217JH

PRINCIPAL DISPLAY PANEL - 600 mg

NDC 71610-499 - Guaifenesin ER 600 mg Tablets